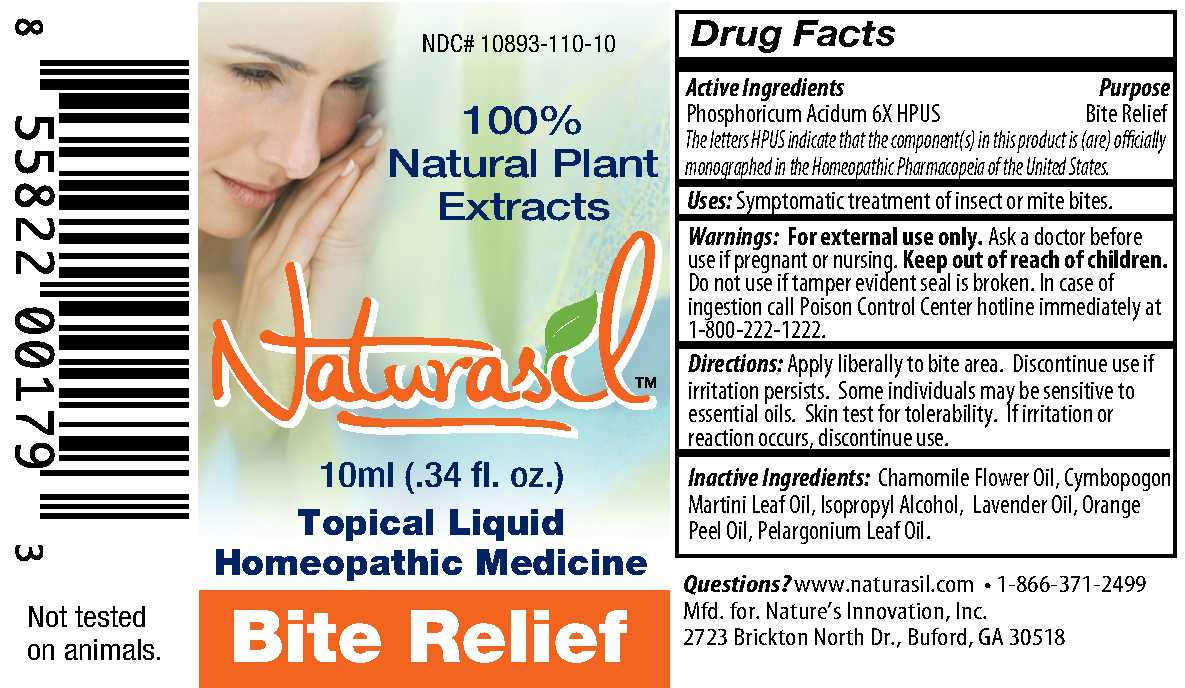 DRUG LABEL: Naturasil
NDC: 10893-110 | Form: LIQUID
Manufacturer: Nature's Innovation, Inc.
Category: homeopathic | Type: HUMAN OTC DRUG LABEL
Date: 20210114

ACTIVE INGREDIENTS: PHOSPHORIC ACID 6 [hp_X]/10 mL
INACTIVE INGREDIENTS: CHAMOMILE FLOWER OIL; PALMAROSA OIL; ISOPROPYL ALCOHOL; LAVENDER OIL; ORANGE OIL; GERANIUM OIL, ALGERIAN TYPE

Bite Relief 10 ml Label

Drug Facts
Active Ingredients
Phosphoricum Acidum 6X HPUS

DESCRIPTION

The letters HPUS indicate that the component(s) in this product is (are) officially monographed in the Homeopathic Pharmacopeia of the United States.

Purpose

Bite Relief

INDICATIONS AND USAGE

Uses: Symptomatic treatment of insect or mite bites.

Warnings: For external use only.

Ask a doctor before use if pregnant or nursing.

Keep out of reach of children.

Do not use if tamper evident seal is broken.

OTHER SAFETY INFORMATION

In case of ingestion call Poison Control Center hotline immediately at 1-800-222-1222.

DOSAGE AND ADMINISTRATION

Directions: Apply liberally to bite area. Discontinue use if irritation persists. Some individuals may be sensitive to essential oils. Skin test for tolerability. If irritation or reaction occurs, discontinue use.

INACTIVE INGREDIENT

Inactive Ingredients: Chamomile Flower Oil, Cymbopogon Martini Leaf Oil, Isopropyl Alcohol, Lavender Oil, Orange Peel Oil, Pelargonium Leaf Oil.

Questions? www.naturasil.com 1-866-371-2499

Mfd. for. Nature's Innovation, Inc.

2723 Brickton North Dr., Buford, GA 30518

ANIMAL PHARMACOLOGY AND OR TOXICOLOGY

Not tested on animals.

PACKAGE LABEL

100% Natural Plant Extracts

Naturasil

10ml (.34 fl. oz.)

Topical Liquid

Homeopathic Medicine

Bite Relief